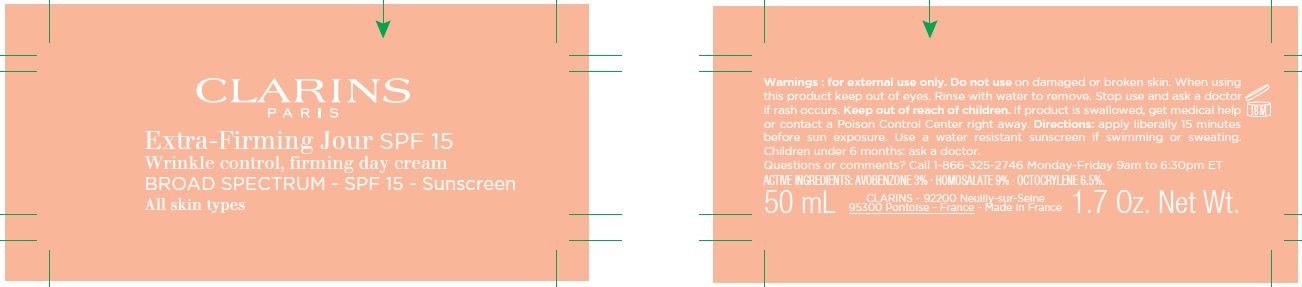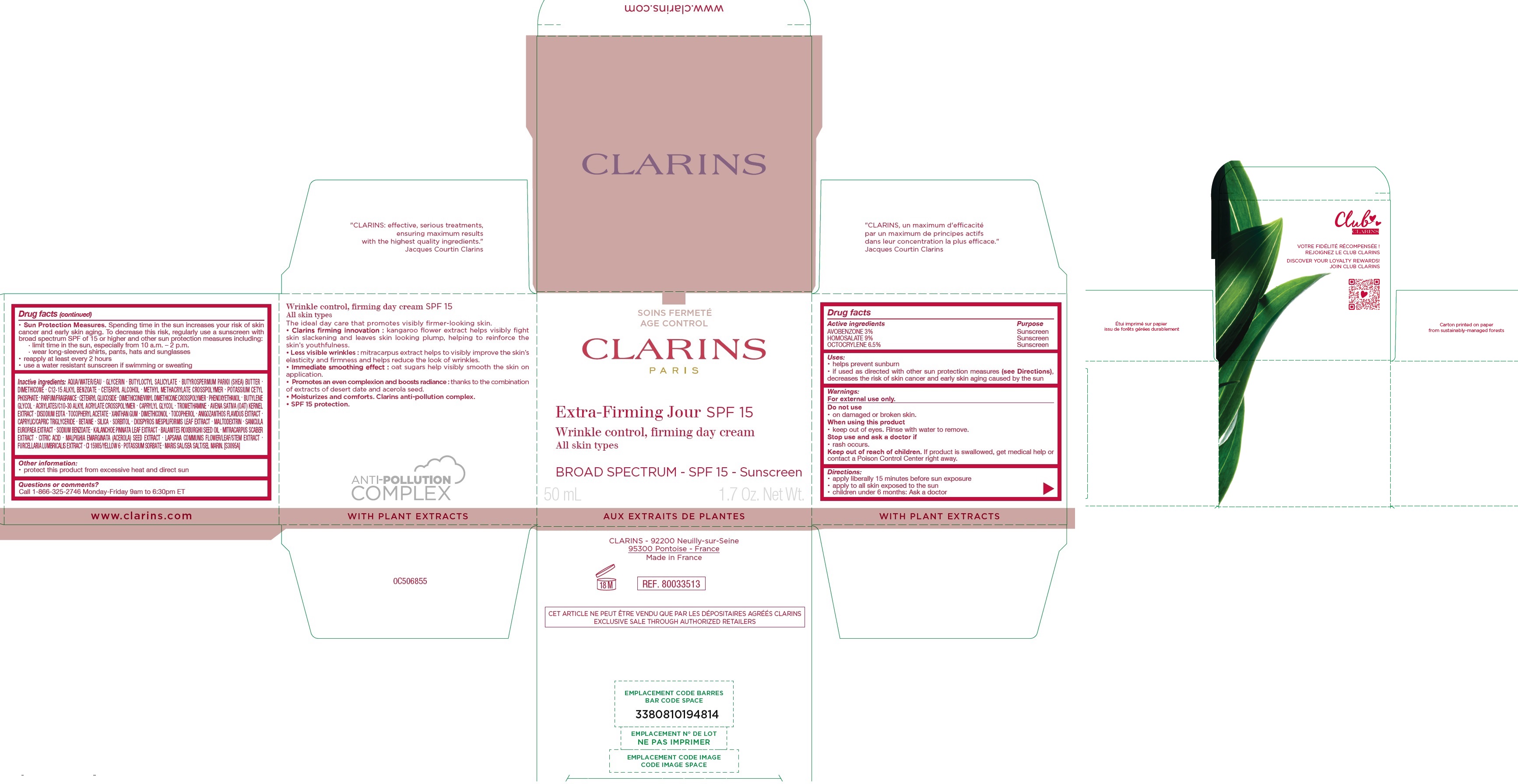 DRUG LABEL: CLARINS - EXTRA-FIRMING JOUR SPF 15 - Wrinkle, Firming Day all skin types - Broad Spectrum SPF 15 Sunscreen
NDC: 58668-9918 | Form: CREAM
Manufacturer: Laboratoires Clarins
Category: otc | Type: HUMAN OTC DRUG LABEL
Date: 20231208

ACTIVE INGREDIENTS: AVOBENZONE 30 mg/1 mL; HOMOSALATE 90 mg/1 mL; OCTOCRYLENE 65 mg/1 mL
INACTIVE INGREDIENTS: WATER; GLYCERIN; BUTYLOCTYL SALICYLATE; SHEA BUTTER; DIMETHICONE; ALKYL (C12-15) BENZOATE; CETOSTEARYL ALCOHOL; POTASSIUM CETYL PHOSPHATE; CETEARYL GLUCOSIDE; PHENOXYETHANOL; BUTYLENE GLYCOL; CAPRYLYL GLYCOL; TROMETHAMINE; OAT; EDETATE DISODIUM ANHYDROUS; .ALPHA.-TOCOPHEROL ACETATE; XANTHAN GUM; TOCOPHEROL; MEDIUM-CHAIN TRIGLYCERIDES; BETAINE; SILICON DIOXIDE; SORBITOL; DIOSPYROS MESPILIFORMIS LEAF; MALTODEXTRIN; SODIUM BENZOATE; KALANCHOE PINNATA LEAF; BALANITES ROXBURGHII SEED OIL; CITRIC ACID MONOHYDRATE; MALPIGHIA EMARGINATA SEED; LAPSANA COMMUNIS FLOWERING TOP; FURCELLERAN; FD&C YELLOW NO. 6; POTASSIUM SORBATE; SEA SALT

CLARINS - EXTRA-FIRMING JOUR SPF 15 - Wrinkle, Firming Day Cream all skin types - Broad Spectrum SPF 15 Sunscreen

Active ingredients

AVOBENZONE 3% HOMOSALATE 9% OCTOCRYLENE 6.5%

Purpose

Sunscreen

Uses:

• helps prevent sunburn • if used as directed with other sun protection measures (see Directions), decreases the risk of skin cancer and early skin aging caused by the sun

Warnings:

For external use only.

Do not use

• on damaged or broken skin.

When using this product

• keep out of eyes. Rinse with water to remove.

Stop use and ask a doctor if

• rash occurs.

Keep out of reach of children.

If product is swallowed, get me dical help or contact a Poison Control Center right away.

Directions:

• apply liberally 15 minutes before sun exposure • apply to all skin exposed to the sun • children under 6 months: Ask a doctor

• Spending time in the sun in creases your risk of skin cancer and early skin aging. To decrease this risk, regularly use a sunscreen with broad spectrum SPF of 15 or higher and other sun protection measures including: • limit time in the sun, especially from 10 a.m. – 2 p.m. • wear long-sleeved shirts, pants, hats and sunglasses • reapply at least every 2 hours • use a water resistant sun screen if swimming or sweating Sun Protection Measures.

Inactive ingredients:

AQUA/WATER/EAU . GLYCERIN . BUTYLOCTYL SALICYLATE . BUTYROSPERMUM PARKII (SHEA) BUTTER . DIMETHICONE . C12-15 ALKYL BENZOATE . CETEARYL ALCOHOL . METHYL METHACRYLATE CROSSPOLYMER . POTASSIUM CETYL PHOSPHATE . PARFUM/FRAGRANCE . CETEARYL GLUCOSIDE . DIMETHICONE/VINYL DIMETHICONE CROSSPOLYMER . PHENOXYETHANOL . BUTYLENE GLYCOL . ACRYLATES/C10-30 ALKYL ACRYLATE CROSSPOLYMER . CAPRYLYL GLYCOL . TROMETHAMINE . AVENA SATIVA (OAT) KERNEL EXTRACT . DISODIUM EDTA . TOCOPHERYL ACETATE . XANTHAN GUM . DIMETHICONOL . TOCOPHEROL . ANIGOZANTHOS FLAVIDUS EXTRACT . CAPRYLIC/CAPRIC TRIGLYCERIDE . BETAINE . SILICA . SORBITOL . DIOSPYROS MESPILIFORMIS LEAF EXTRACT . MALTODEXTRIN . SANICULA EUROPAEA EXTRACT . SODIUM BENZOATE . KALANCHOE PINNATA LEAF EXTRACT . BALANITES ROXBURGHII SEED OIL . MITRACARPUS SCABER EXTRACT . CITRIC ACID . MALPIGHIA EMARGINATA (ACEROLA) SEED EXTRACT . LAPSANA COMMUNIS FLOWER/LEAF/STEM EXTRACT . FURCELLARIA LUMBRICALIS EXTRACT . CI 15985/YELLOW 6 . POTASSIUM SORBATE . MARIS SAL/SEA SALT/SEL MARIN. [S3095A]

Other information:

• protect this product from excessive heat and direct sun

Questions or comments?

Call 1-866-325-2746 Monday-Friday 9am to 6:30pm ET